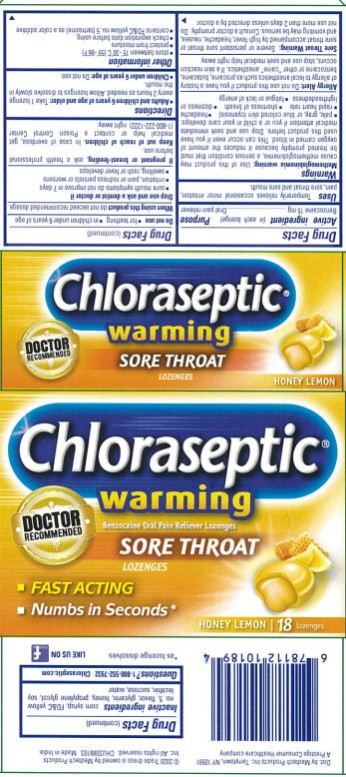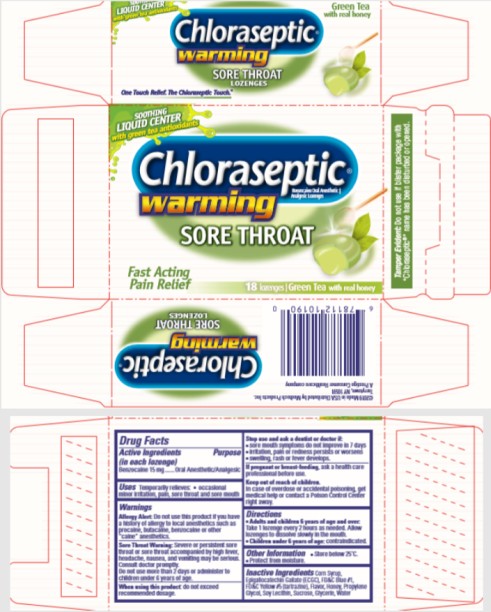 DRUG LABEL: Chloraseptic Warming Sore Throat
NDC: 67172-018 | Form: LOZENGE
Manufacturer: Prestige Brands Holdings, Inc.
Category: otc | Type: HUMAN OTC DRUG LABEL
Date: 20251023

ACTIVE INGREDIENTS: BENZOCAINE 15 mg/1 1
INACTIVE INGREDIENTS: CORN SYRUP; EPIGALLOCATECHIN GALLATE; FD&C BLUE NO. 1; FD&C YELLOW NO. 5; HONEY; PROPYLENE GLYCOL; LECITHIN, SOYBEAN; SUCROSE; GLYCERIN; WATER

Chloraseptic Green Tea Lozenges

[Chloraseptic© Warming Sore Throat Lozenges – Honey ]

Drug Facts

Active ingredient

(in each lozenge)

Benzocaine 15 mg

Purpose

Oral Anesthetic/Analgesic

Uses

Temporarily relieves occasional minor irritation, pain, sore throat and sore mouth

Warnings

Methemoglobinemia warning:

Use of this product may cause methemoglobinemia, a serious condition that must be treated promptly because it reduces the amount of oxygen carried in blood. This can occur even if you have used this product before. Stop use and seek immediate medical attention if you or a child in your care develops:

∙ pale, gray, or blue colored skin (cyanosis)

∙ headache

∙ rapid heart rate

∙ shortness of breath

∙ dizziness or lightheadedness

∙ fatigue or lack of energy

Allergy Alert: Do not use this product if you have a history of allergy to local anesthetics such as procaine, butacaine, benzocaine or other “caine” anesthetics. If a skin reaction occurs, stop use and seek medical help right away.

Sore Throat Warning: Severe or persistent sore throat or sore throat accompanied by high fever, headache, nausea and vomiting may be serious. Consult a doctor promptly. Do not use more than 2 days unless directed by a doctor.

Do not use:

- for teething
- in children under 6 years of age

Stop use and ask a dentist or doctor if

- sore mouth symptoms do not improve in 7 days
- irritation, pain or redness persists or worsens
- swelling, rash or fever develops

Keep out of reach of children.

In case of overdose or accidental poisoning, get medical help or contact a Poison Control Center (1-800-222-1222) right away.

Directions

- Adults and children 6 years of age and over: Take 1 lozenge every 2 hours as needed. Allow lozenges to dissolve slowly in the mouth.
- Children under 6 years of age: Do not use.

Other information

- Store between 15ºC - 30ºC (59ºF and 86ºF)
- Protect from moisture.
- Check expiration date before using.
- Contains FD&C yellow no. 5 (tartrazine) as a color additive.

Inactive ingredients

corn syrup, FD&C yellow no. 5, flavor, glycerin, honey, propylene glycol, soy lecithin, sucrose, water

Questions?

1-800-552-7932 Chloraseptic.com

PRINCIPAL DISPLAY PANEL

Chloraseptic© Warming Sore Throat Lozenges
Benzocaine Oral Anesthetic | Analgesic
18 lozenges | Honey Lemon

PRINCIPAL DISPLAY PANEL

Chloraseptic© Warming Sore Throat Lozenges
Benzocaine Oral Anesthetic | Analgesic
18 lozenges | Green Tea